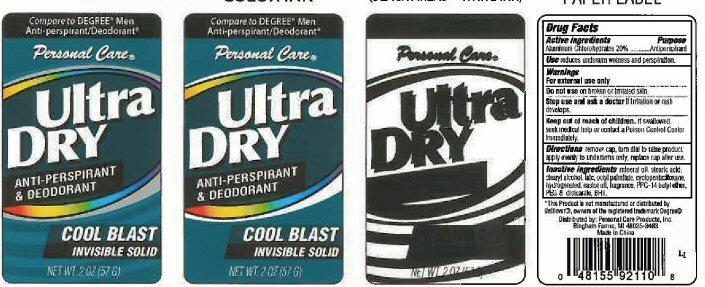 DRUG LABEL: Ultra dry antiperspirant
                        
NDC: 29500-9211 | Form: CREAM
Manufacturer: Personal Care Products
Category: otc | Type: HUMAN OTC DRUG LABEL
Date: 20130904

ACTIVE INGREDIENTS: ALUMINUM CHLOROHYDRATE 11.4 g/57 g
INACTIVE INGREDIENTS: MINERAL OIL; STEARIC ACID; STEARYL ALCOHOL; TALC; ETHYLHEXYL PALMITATE; CYCLOMETHICONE 5; CASTOR OIL; PPG-14 BUTYL ETHER; PEG-8 DISTEARATE; BUTYLATED HYDROXYTOLUENE

Ultra Dry Anti perspirant and deodorant

Active Ingredients Aluminum Chlorohydrates 20%

Purpose Antiperspirant

Keep out of reach of children. If swallowed, seek medical help or contact a Poison Control Center immediately.

INDICATIONS AND USAGE

Uses reduces underarm wetness and perspiration.

Warnings

For external use only

Stop use and ask a doctor if irritation or rash develops.

Directions

Remove cap, turn dial to raise product, apply evenly to underarms only, replace cap after use.

INACTIVE INGREDIENT

Inactive Ingredients mineral oil, stearic acid, stearyl alcohol, talc, octyl palmitate, cyclopentasiloxane, hydrogenated, castor oil, fragrance, PPF-14 butyl ehter, PEG-8 distearate, BHT.

PACKAGE LABEL

Compare to Degree Men

anti-perspirant/deodorant

Personal Care

Ultra Dry Anti-perspirant and deodorant

Cool blast Invisible solid

Net wt. 2 oz (57 g)